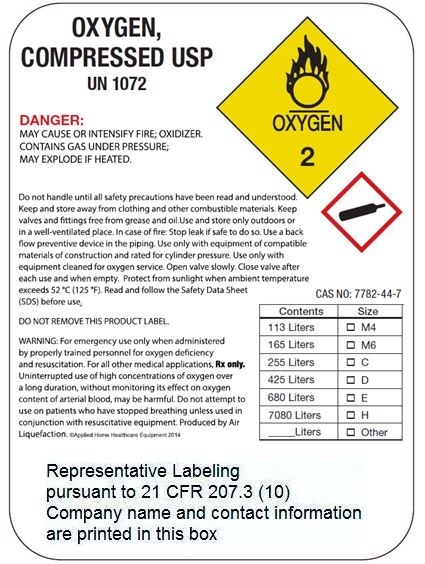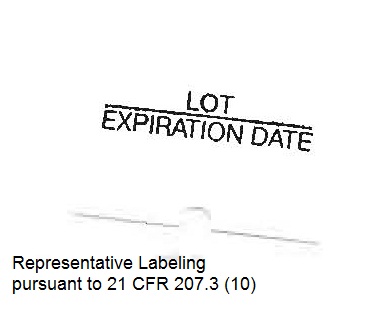 DRUG LABEL: Oxygen
NDC: 73544-001 | Form: GAS
Manufacturer: MasVida Health Care Solutions, LLC
Category: prescription | Type: HUMAN PRESCRIPTION DRUG LABEL
Date: 20260129

ACTIVE INGREDIENTS: OXYGEN 99 L/100 L

Oxygen, USP

Principal for Oxygen Product

OXYGEN

COMPRESSED

USP

UN 1072

PRODUCED BY AIR LIQUIFICATION

WARNING: HIGH PRESSURE OXIDIZING GAS, VIGOROUSLY ACCELERATES COMBUSTION. NO SMOKING IN THE PRESENCE OF OXYGEN OR A FIRE MAY RESULT.

WARNING: For emergency use only when administered by properly trained personnel for oxygen deficiency and resuscitation. For all other medical applications, Rx only.

WARNING: Federal law prohibits dispensing without prescription. Uninterrupted use of high concentrations of oxygen over a long duration, without monitoring its effect on oxygen content of arterial blood, may be harmful. Use only with pressure reducing equipment and apparatus designed for oxygen. Do not attempt to use on patients who have stopped breathing, unless used in conjuction with resuscitative equipment.

WARNING: Keep oil and grease away. Use only with equipment cleaned for oxygen service and rated for cylinder pressure. Open valve slowly. Close valve after each use and when empty.

USE IN ACCORDANCE WITH MATERIAL SAFETY DATA SHEET.

DO NOT REMOVE THIS PRODUCT LABEL.